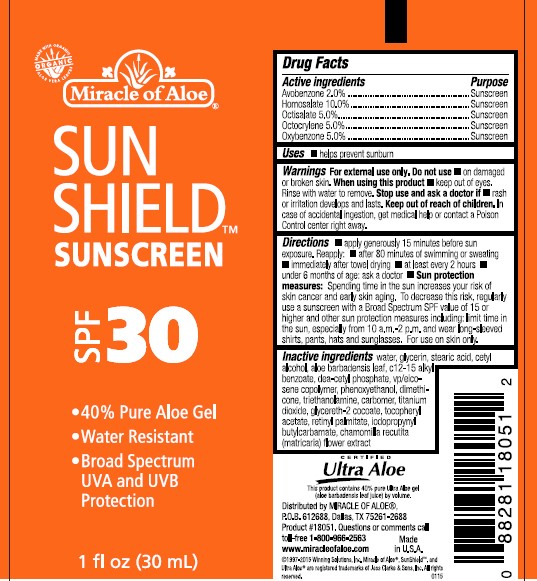 DRUG LABEL: SUN SHIELD SUNSCREEN
NDC: 66391-3001 | Form: LOTION
Manufacturer: Winning Solutions
Category: otc | Type: HUMAN OTC DRUG LABEL
Date: 20230126

ACTIVE INGREDIENTS: HOMOSALATE 10 g/100 mL; OXYBENZONE 5 g/100 mL; OCTISALATE 5 g/100 mL; OCTOCRYLENE 5 g/100 mL; AVOBENZONE 2 g/100 mL
INACTIVE INGREDIENTS: STEARIC ACID; GLYCERETH-2 COCOATE; ALKYL (C12-15) BENZOATE; VITAMIN A PALMITATE; MATRICARIA CHAMOMILLA FLOWERING TOP; TROLAMINE; WATER; GLYCERIN; ALOE VERA LEAF; DIETHANOLAMINE CETYL PHOSPHATE; PHENOXYETHANOL; .ALPHA.-TOCOPHEROL ACETATE; IODOPROPYNYL BUTYLCARBAMATE; VINYLPYRROLIDONE/EICOSENE COPOLYMER; CARBOMER HOMOPOLYMER, UNSPECIFIED TYPE; DIMETHICONE; TITANIUM DIOXIDE; CETYL ALCOHOL

Winning Solutions (as PLD) - Sun Shield Sunscreen SPF 30 (66391-3001)

Active Ingredient

AVOBENZONE 2.0%

HOMOSALATE 10.0%

OCTISALATE 5.0%

OCTOCRYLENE 5.0%

OXYBENZONE 5.0%

Purpose

SUNSCREEN

Uses

- HELPS PREVENT SUNBURN

Warnings

For external use only.

Do not use

- on damaged or broken skin.

When using this product

- keep out of eyes. Rinse with water to remove.

Stop use and ask a doctor if

- rash or irritation develops and lasts.

Keep out of reach of children. In case of accidental ingestion, get medical help or contact a Poison Control center right away.

Directions

- apply generously 15 minutes before sun exposure.

Reapply:

- after 80 minutes of swimming or sweating
- immediately after towel drying
- at least every 2 hours
- under 6 months of age: ask a doctor

- Sun protection measures: Spending time in the sun increases your risk of skin cancer and early skin aging. To decrease this risk, regularly use a sunscreen with a Broad Spectrum SPF value of 15 or higher and other sun protection measures including: limit time in the sun, especially from 10 a.m.-2 p.m. and wear long-sleeved shirts, pants, hats and sunglasses. For use on skin only.

Inactive ingredients

water, glycerin, stearic acid, cetyl alcohol, aloe barbadensis leaf, c12-15 alkyl benzoate, dea-cetyl phosphate, vp/eicosene copolymer, phenoxyethanol, dimethicone, triethanolamine, carbomer, titanium dioxide, glycereth-2 cocoate, tocopheryl acetate, retinyl palmitate, iodopropynyl butylcarbamate, chamomilla recutitita (matricaria) flower extract